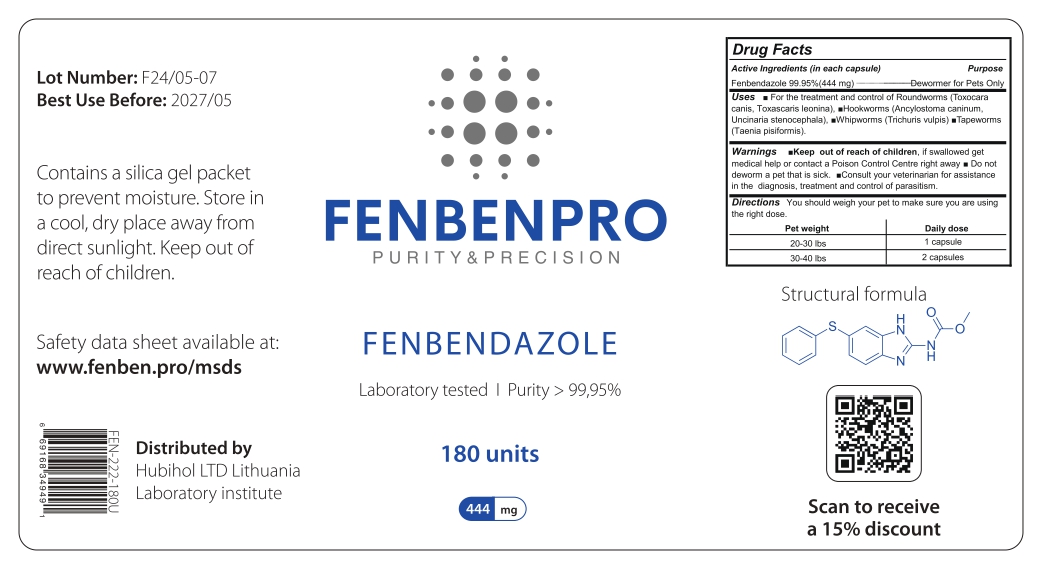 DRUG LABEL: FENBENPRO PURITY and PRECISION FENBENDAZOLE
NDC: 86217-0011 | Form: CAPSULE
Manufacturer: HUBIHOL, UAB
Category: animal | Type: OTC ANIMAL DRUG LABEL
Date: 20250303

ACTIVE INGREDIENTS: FENBENDAZOLE 444 mg/180 U

FENBENPRO PURITY and PRECISION FENBENDAZOLE

Active Ingredients

Active Ingredients (in each capsule)

Fenbendazole 99.95% (444 mg)

Package Labeling

Lot Number: F24/05-07 Best Use Before: 2027/05
Contains a silica gel packet to prevent moisture. Store in a cool, dry place away from direct sunlight. Keep out of reach of children.
Safety data sheet available at: www.fenben.pro/msds
Distributed by
Hubihol LTD Lithuania Laboratory institute
FENBENPRO
PURITY & PRECISION
FENBENDAZOLE
Laboratory tested I Purity> 99,95%
180 units
444 mg
Drug Facts
Active Ingredients (in each capsule) Fenbendazole 99.95% (444 mg)
Uses
Purpose Dewormer for Pets Only
For the treatment and control of Roundworms (Toxocara canis, Toxascaris leonina), ■Hookworms (Ancylostoma caninum, Uncinaria stenocephala), Whipworms (Trichuris vulpis) ■Tapeworms (Taenia pisiformis).
Warnings Keep out of reach of children, if swallowed get medical help or contact a Poison Control Centre right away■ Do not deworm a pet that is sick. Consult your veterinarian for assistance in the diagnosis, treatment and control of parasitism. Directions You should weigh your pet to make sure you are using the right dose.
Pet weight 20-30 lbs
30-40 lbs
Daily dose
1 capsule
Structural formula
2 capsules
Scan to receive
a 15% discount